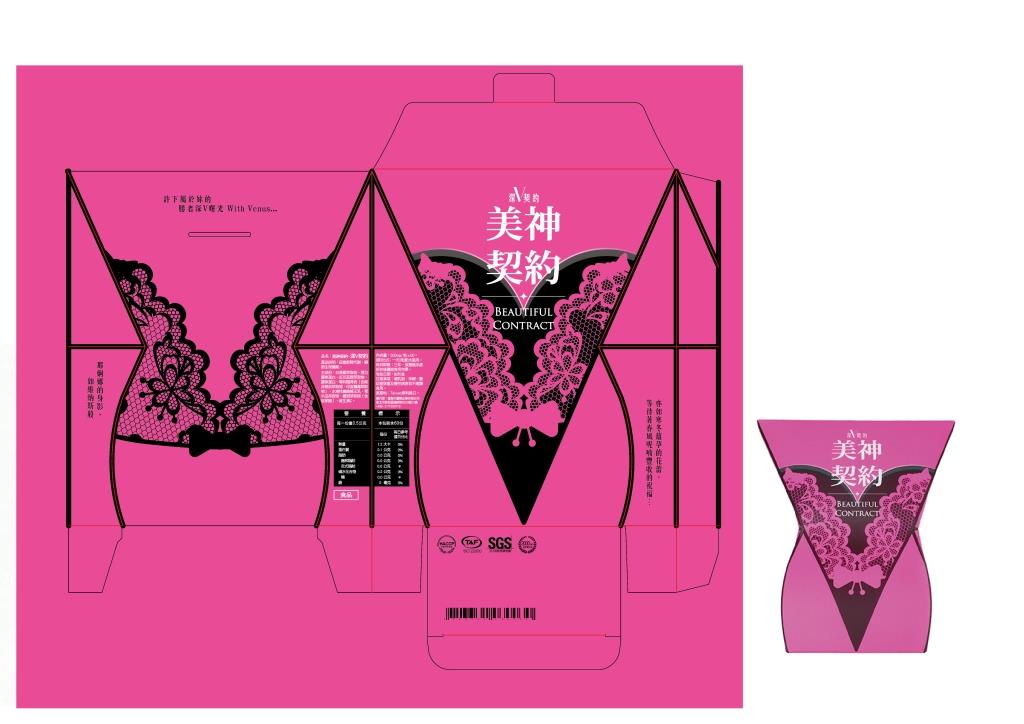 DRUG LABEL: BEAUTIFUL CONTRACT - Deep V Breast contract
NDC: 70470-9952 | Form: CAPSULE, GELATIN COATED
Manufacturer: Phytopia Co., Ltd.
Category: homeopathic | Type: HUMAN OTC DRUG LABEL
Date: 20170201

ACTIVE INGREDIENTS: PAPAIN 35 mg/500 mg
INACTIVE INGREDIENTS: ELASTIN (HUMAN); PUERARIA MONTANA VAR. LOBATA WHOLE; MALTODEXTRIN; PHYLLANTHUS EMBLICA FRUIT; WITHANIA SOMNIFERA WHOLE; ROYAL JELLY; ASCORBIC ACID; HYALURONIC ACID; HYDROLYSED MARINE COLLAGEN (ENZYMATIC; 2000 MW); RED CLOVER

Drug Facts

Papain from Green papaya extract 35mg

Use

To increase the growth and firming of breast.

Dosage Suggestion

2 capsules maximum per day

INACTIVE INGREDIENT

Other Ingredients

Pueraria montana var. lobata whole, Elastin, Red clover extract, Hydrolysed marine collagen, Sendara(Standaraized extract of Withania somnifera and phyllanthus emblica), Fibersol-2 (maltodextrin), Royal jelly, Hyaluronic Acid from Cockscomb extract powder, Ascorbic Acid from VITAMIN C.

Directions

Take two capsule a day, and drink water.

Warnings

For external use only. Stop use and ask doctor if rash occurs. Keep out reach of children.

Other Information

Protect this product from excessive heat

and direct sun.

Warnings

For external use only. Stop use and ask doctor if rash occurs. Keep out reach of children.